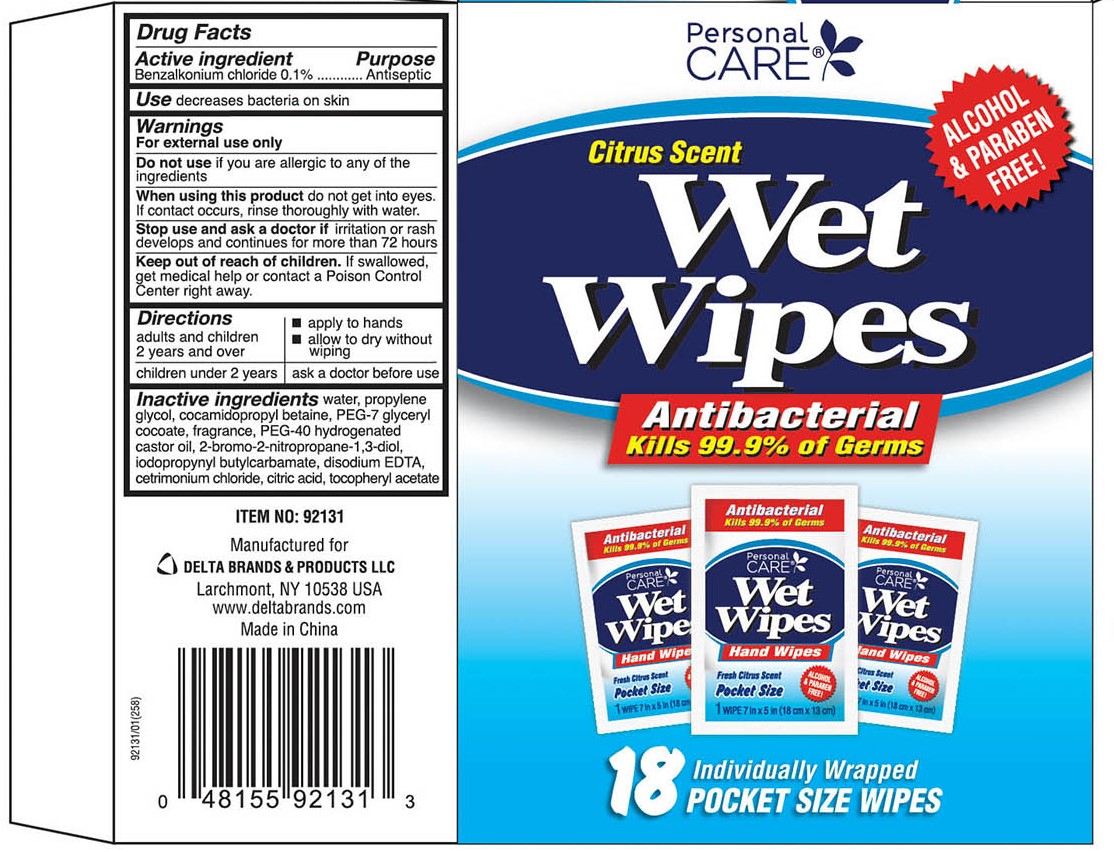 DRUG LABEL: Personal CARE
NDC: 72133-434 | Form: CLOTH
Manufacturer: Delta Brands & Products, LLC
Category: otc | Type: HUMAN OTC DRUG LABEL
Date: 20180507

ACTIVE INGREDIENTS: BENZALKONIUM CHLORIDE 0.1 g/1 1
INACTIVE INGREDIENTS: WATER; PROPYLENE GLYCOL; COCAMIDOPROPYL BETAINE; PEG-7 GLYCERYL COCOATE; BRONOPOL; IODOPROPYNYL BUTYLCARBAMATE; EDETATE DISODIUM ANHYDROUS; CETRIMONIUM CHLORIDE; CITRIC ACID MONOHYDRATE; ALPHA-TOCOPHEROL ACETATE; POLYOXYL 40 HYDROGENATED CASTOR OIL

Drug Facts

Active Ingredient

Benzalkonium Chloride 0.1%

Purpose

Antiseptic

Uses

decreases bacteria on the skin

Warnings

For external use only

Do not use

if you are allergic to any of the ingredients

When using this product

do not get into eyes. If contact occurs, rinse thoroughly with water.

Stop use and ask a doctor if

irritation or rash develops and continues for more than 72 hours

Keep out of reach of children

If swallowed get medical help or contact a Poison Control Center right away.

Directions

adults and children 2 years and over ■ apply to hands

■ allow to dry without wiping.

children under 2 years ask a doctor before use.

Inactive Ingredients

water, propylene glycol, cocamidopropyl betaine, PEG-7 glyceryl cocoate, fragrance, PEG-40 hydrogenated castor oil, 2-bromo-2-nitropropane-1,3-diol, iodopropynyl butacarbamate, disodium EDTA, cetrimonium chloride, citric acid, tocopheryl acetate